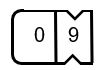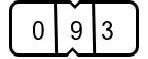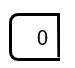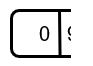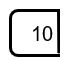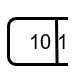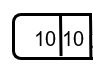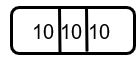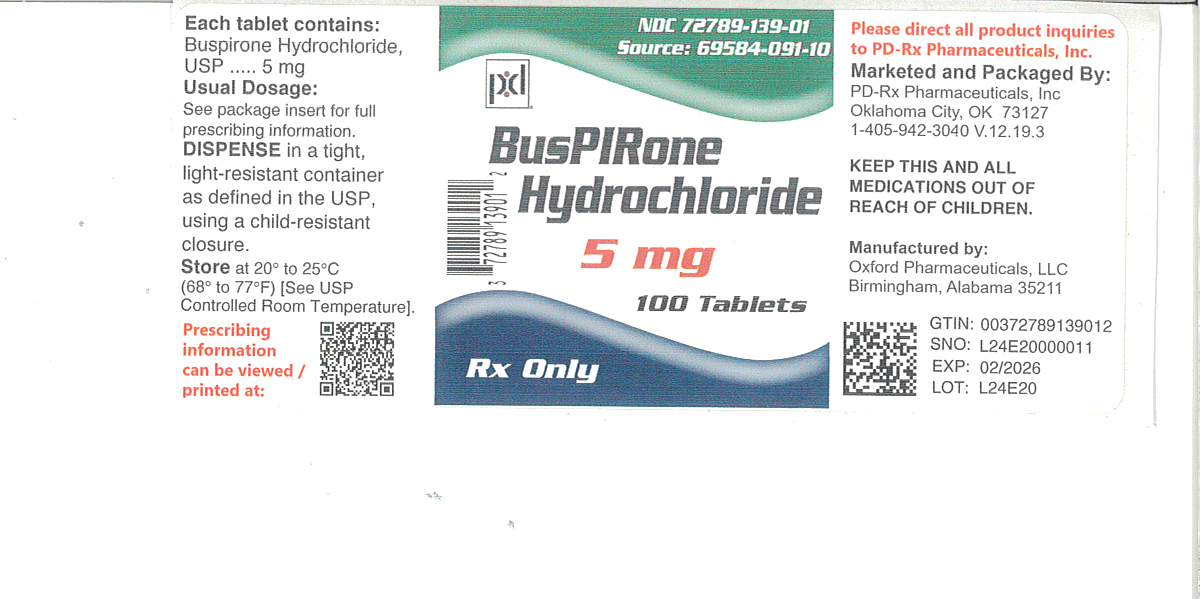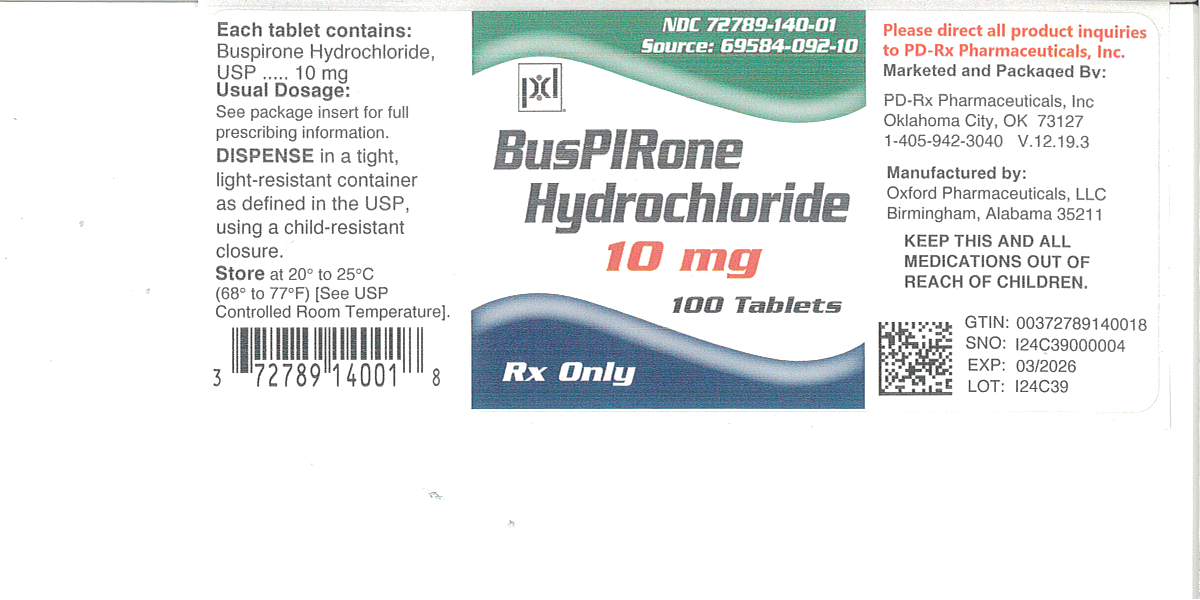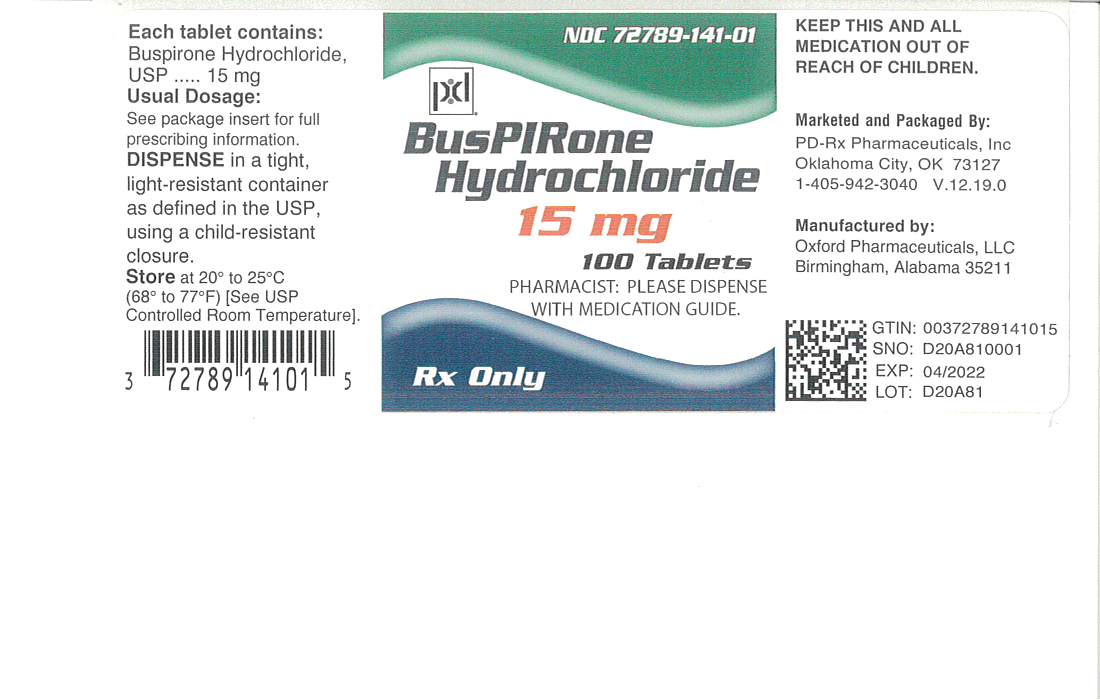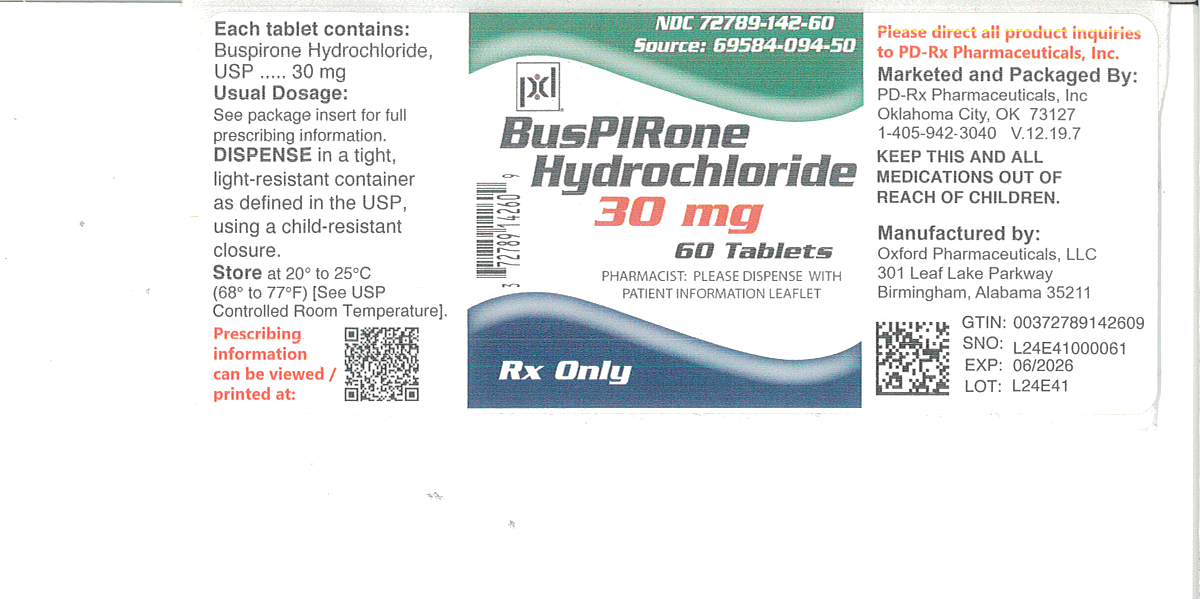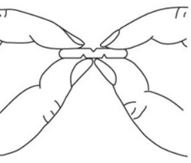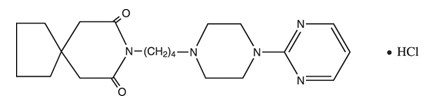 DRUG LABEL: Buspirone Hydrochloride
NDC: 72789-139 | Form: TABLET
Manufacturer: PD-Rx Pharmaceuticals, Inc.
Category: prescription | Type: HUMAN PRESCRIPTION DRUG LABEL
Date: 20260224

ACTIVE INGREDIENTS: BUSPIRONE HYDROCHLORIDE 5 mg/1 1
INACTIVE INGREDIENTS: SILICON DIOXIDE; ANHYDROUS LACTOSE; MAGNESIUM STEARATE; MICROCRYSTALLINE CELLULOSE 102; SODIUM STARCH GLYCOLATE TYPE A POTATO

Buspirone Hydrochloride Tablets USP
(Patient Information Sheet Included)

Rx only

DESCRIPTION

Buspirone hydrochloride tablets, USP is an antianxiety agent that is not chemically or pharmacologically related to the benzodiazepines, barbiturates, or other sedative/anxiolytic drugs.

Buspirone hydrochloride is a white crystalline, water soluble compound with a molecular weight of 422.0. Chemically, buspirone hydrochloride is 8-[4-[4-(2-pyrimidinyl)-1-piperazinyl]butyl]-8-azaspiro[4.5]decane-7,9-dione monohydrochloride. The empirical formula C21H31N5O2• HCl is represented by the following structural formula:

Buspirone hydrochloride, USP is supplied as tablets for oral administration containing 5 mg, 10 mg, 15 mg, or 30 mg of buspirone hydrochloride, USP (equivalent to 4.6 mg, 9.1 mg, and 13.7 mg and 27.4 mg of buspirone free base, respectively). The 5-mg and 10-mg tablets are scored so they can be bisected. Thus, the 5-mg tablet can also provide a 2.5-mg dose, and the 10-mg tablet can provide a 5-mg dose. The 15-mg and 30-mg tablets are provided in the adjustable dosage tablet design. These tablets are scored so they can be either bisected or trisected. Thus, a single 15-mg tablet can provide the following doses: 15 mg (entire tablet), 10 mg (two thirds of a tablet), 7.5 mg (one half of a tablet), or 5 mg (one third of a tablet). A single 30-mg tablet can provide the following doses: 30 mg (entire tablet), 20 mg (two thirds of a tablet), 15 mg (one half of a tablet), or 10 mg (one third of a tablet). Buspirone hydrochloride, USP tablets contain the following inactive ingredients: colloidal silicon dioxide, lactose anhydrous, magnesium stearate, microcrystalline cellulose, and sodium starch glycolate (Type A).

CLINICAL PHARMACOLOGY

The mechanism of action of buspirone is unknown. Buspirone differs from typical benzodiazepine anxiolytics in that it does not exert anticonvulsant or muscle relaxant effects. It also lacks the prominent sedative effect that is associated with more typical anxiolytics. In vitropreclinical studies have shown that buspirone has a high affinity for serotonin (5-HT1A) receptors. Buspirone has no significant affinity for benzodiazepine receptors and does not affect GABA binding in vitroor in vivowhen tested in preclinical models.

Buspirone has moderate affinity for brain D2-dopamine receptors. Some studies do suggest that buspirone may have indirect effects on other neurotransmitter systems.

Buspirone hydrochloride tablets, USP are rapidly absorbed in man and undergo extensive first-pass metabolism. In a radiolabeled study, unchanged buspirone in the plasma accounted for only about 1% of the radioactivity in the plasma. Following oral administration, plasma concentrations of unchanged buspirone are very low and variable between subjects. Peak plasma levels of 1 ng/mL to 6 ng/mL have been observed 40 to 90 minutes after single oral doses of 20 mg. The single-dose bioavailability of unchanged buspirone when taken as a tablet is on the average about 90% of an equivalent dose of solution, but there is large variability.

The effects of food upon the bioavailability of buspirone hydrochloride tablets, USP have been studied in eight subjects. They were given a 20-mg dose with and without food; the area under the plasma concentration-time curve (AUC) and peak plasma concentration (Cmax) of unchanged buspirone increased by 84% and 116%, respectively, but the total amount of buspirone immunoreactive material did not change. This suggests that food may decrease the extent of presystemic clearance of buspirone (see DOSAGE AND ADMINISTRATION).

A multiple-dose study conducted in 15 subjects suggests that buspirone has nonlinear pharmacokinetics. Thus, dose increases and repeated dosing may lead to somewhat higher blood levels of unchanged buspirone than would be predicted from results of single-dose studies.

An in vitroprotein binding study indicated that approximately 86% of buspirone is bound to plasma proteins. It was also observed that aspirin increased the plasma levels of free buspirone by 23%, while flurazepam decreased the plasma levels of free buspirone by 20%. However, it is not known whether these drugs cause similar effects on plasma levels of free buspirone in vivo, or whether such changes, if they do occur, cause clinically significant differences in treatment outcome. An in vitrostudy indicated that buspirone did not displace highly protein-bound drugs such as phenytoin, warfarin, and propranolol from plasma protein, and that buspirone may displace digoxin.

Buspirone is metabolized primarily by oxidation, which in vitrohas been shown to be mediated by cytochrome P450 3A4 (CYP3A4) (see PRECAUTIONS: Drug Interactions). Several hydroxylated derivatives and a pharmacologically active metabolite, 1-pyrimidinylpiperazine (1-PP), are produced. In animal models predictive of anxiolytic potential, 1-PP has about one quarter of the activity of buspirone, but is present in up to 20-fold greater amounts. However, this is probably not important in humans: blood samples from humans chronically exposed to buspirone hydrochloride do not exhibit high levels of 1-PP; mean values are approximately 3 ng/mL and the highest human blood level recorded among 108 chronically dosed patients was 17 ng/mL, less than 1/200th of 1-PP levels found in animals given large doses of buspirone without signs of toxicity.

In a single-dose study using^14C-labeled buspirone, 29% to 63% of the dose was excreted in the urine within 24 hours, primarily as metabolites; fecal excretion accounted for 18% to 38% of the dose. The average elimination half-life of unchanged buspirone after single doses of 10 to 40 mg is about 2 to 3 hours.

Special Populations

Age and Gender Effects

After single or multiple doses in adults, no significant differences in buspirone pharmacokinetics (AUC and Cmax) were observed between elderly and younger subjects or between men and women.

Hepatic Impairment

After multiple-dose administration of buspirone to patients with hepatic impairment, steady-state AUC of buspirone increased 13-fold compared with healthy subjects (see PRECAUTIONS).

Renal Impairment

After multiple-dose administration of buspirone to renally impaired (Clcr= 10 to 70 mL/min/1.73 m^2) patients, steady-state AUC of buspirone increased 4-fold compared with healthy (Clcr≥ 80 mL/min/1.73 m^2) subjects (see PRECAUTIONS).

Race Effects

The effects of race on the pharmacokinetics of buspirone have not been studied.

INDICATIONS AND USAGE

Buspirone hydrochloride tablets, USP are indicated for the management of anxiety disorders or the short-term relief of the symptoms of anxiety. Anxiety or tension associated with the stress of everyday life usually does not require treatment with an anxiolytic.

The efficacy of buspirone hydrochloride tablets, USP has been demonstrated in controlled clinical trials of outpatients whose diagnosis roughly corresponds to Generalized Anxiety Disorder (GAD). Many of the patients enrolled in these studies also had coexisting depressive symptoms and buspirone hydrochloride tablets, USP relieved anxiety in the presence of these coexisting depressive symptoms. The patients evaluated in these studies had experienced symptoms for periods of 1 month to over 1 year prior to the study, with an average symptom duration of 6 months. Generalized Anxiety Disorder (300.02) is described in the American Psychiatric Association’s Diagnostic and Statistical Manual, III^1as follows:

Generalized, persistent anxiety (of at least 1 month continual duration), manifested by symptoms from three of the four following categories:

1. Motor tension: shakiness, jitteriness, jumpiness, trembling, tension, muscle aches, fatigability, inability to relax, eyelid twitch, furrowed brow, strained face, fidgeting, restlessness, easy startle.
2. Autonomic hyperactivity: sweating, heart pounding or racing, cold, clammy hands, dry mouth, dizziness, lightheadedness, paresthesias (tingling in hands or feet), upset stomach, hot or cold spells, frequent urination, diarrhea, discomfort in the pit of the stomach, lump in the throat, flushing, pallor, high resting pulse and respiration rate.
3. Apprehensive expectation: anxiety, worry, fear, rumination, and anticipation of misfortune to self or others.
4. Vigilance and scanning: hyperattentiveness resulting in distractibility, difficulty in concentrating, insomnia, feeling "on edge," irritability, impatience.

The above symptoms would not be due to another mental disorder, such as a depressive disorder or schizophrenia. However, mild depressive symptoms are common in GAD.

The effectiveness of buspirone hydrochloride tablets, USP in long-term use, that is, for more than 3 to 4 weeks, has not been demonstrated in controlled trials. There is no body of evidence available that systematically addresses the appropriate duration of treatment for GAD. However, in a study of long-term use, 264 patients were treated with buspirone hydrochloride tablets, USP for 1 year without ill effect. Therefore, the physician who elects to use buspirone hydrochloride tablets, USP for extended periods should periodically reassess the usefulness of the drug for the individual patient.

CONTRAINDICATIONS

Buspirone hydrochloride tablets, USP are contraindicated in patients hypersensitive to buspirone hydrochloride.

The use of monoamine oxidase inhibitors (MAOIs) intended to treat depression with buspirone or within 14 days of stopping treatment with buspirone is contraindicated because of an increased risk of serotonin syndrome and/or elevated blood pressure. The use of buspirone within 14 days of stopping an MAOI intended to treat depression is also contraindicated.

Starting buspirone in a patient who is being treated with reversible MAOIs such as linezolid or intravenous methylene blue is also contraindicated because of an increased risk of serotonin syndrome. (see WARNINGS, DOSAGE AND ADMINISTRATIONAND DRUG INTERACTIONS).

WARNINGS

The administration of buspirone hydrochloride tablets, USP to a patient taking a monoamine oxidase inhibitor (MAOI) may pose a hazard.There have been reports of the occurrence of elevated blood pressure when buspirone hydrochloride, USP has been added to a regimen including an MAOI. Therefore, it is recommended that buspirone hydrochloride tablets, USP not be used concomitantly with an MAOI.

Serotonin Syndrome

The development of a potentially life-threatening serotonin syndrome has been reported with SNRIs SSRIs, and other serotonergic drugs, including buspirone, alone but particularly with concomitant use of other serotonergic drugs (including triptans), with drugs that impair metabolism of serotonin (in particular, MAOIs, including reversible MAOIs such as linezolid and intravenous methylene blue), or with antipsychotics or other dopamine antagonists.

Serotonin syndrome symptoms may include mental status changes (e.g., agitation, hallucinations, delirium, and coma), autonomic instability (e.g., tachycardia, labile blood pressure, dizziness, diaphoresis, flushing, hyperthermia), neuromuscular changes (e.g., tremor, rigidity, myoclonus, hyperreflexia, incoordination), seizures, and/or gastrointestinal symptoms (e.g., nausea, vomiting, diarrhea). Patients should be monitored for emergence of serotonin syndrome.

The concomitant use of buspirone with MAOIs intended to treat depression is contraindicated. Buspirone should also not be started in a patient who is being treated with reversible MAOIs such as linezolid or intravenous methylene blue. All reports with methylene blue that provided information on the route of administration involved intravenous administration in the dose range of 1 mg/kg to 8 mg/kg. There have been no reports involving the administration of methylene blue by other routes (such as oral tablets or local tissue injection) or at lower doses. There may be circumstances when it is necessary to initiate treatment with a reversible MAOI such as linezolid or intravenous methylene blue in a patient taking buspirone. Buspirone should be discontinued before initiating treatment with the reversible MAOI [see CONTRAINDICATIONS, DOSAGE AND ADMINISTRATIONAND DRUG INTERACTIONS].

If concomitant use of buspirone with a 5-hydroxytryptmine receptor agonist (triptan) is clinically warranted, careful observation of the patient is advised, particularly during treatment initiation and dose increases.

The concomitant use of buspirone with serotonin precursors (such as tryptophan) is not recommended.

Treatment with buspirone and any concomitant serotonergic or antidopaminergic agents, including antipsychotics, should be discontinued immediately if the above events occur and supportive symptomatic treatment should be initiated.

Because buspirone hydrochloride tablets, USP have no established antipsychotic activity, it should not be employed in lieu of appropriate antipsychotic treatment.

PRECAUTIONS General

GENERAL PRECAUTIONS

Interference with Cognitive and Motor Performance

Studies indicate that buspirone hydrochloride tablets, USP are less sedating than other anxiolytics and that it does not produce significant functional impairment. However, its CNS effects in any individual patient may not be predictable. Therefore, patients should be cautioned about operating an automobile or using complex machinery until they are reasonably certain that buspirone treatment does not affect them adversely.

While formal studies of the interaction of buspirone hydrochloride, USP with alcohol indicate that buspirone does not increase alcohol-induced impairment in motor and mental performance, it is prudent to avoid concomitant use of alcohol and buspirone.

Potential for Withdrawal Reactions in Sedative/Hypnotic/Anxiolytic Drug-Dependent Patients

Because buspirone hydrochloride tablets, USP do not exhibit cross-tolerance with benzodiazepines and other common sedative/hypnotic drugs, it will not block the withdrawal syndrome often seen with cessation of therapy with these drugs. Therefore, before starting therapy with buspirone hydrochloride tablets, USP, it is advisable to withdraw patients gradually, especially patients who have been using a CNS-depressant drug chronically, from their prior treatment. Rebound or withdrawal symptoms may occur over varying time periods, depending in part on the type of drug, and its effective half-life of elimination.

The syndrome of withdrawal from sedative/hypnotic/anxiolytic drugs can appear as any combination of irritability, anxiety, agitation, insomnia, tremor, abdominal cramps, muscle cramps, vomiting, sweating, flu-like symptoms without fever, and occasionally, even as seizures.

Possible Concerns Related to Buspirone’s Binding to Dopamine Receptors

Because buspirone can bind to central dopamine receptors, a question has been raised about its potential to cause acute and chronic changes in dopamine-mediated neurological function (e.g., dystonia, pseudo-parkinsonism, akathisia, and tardive dyskinesia). Clinical experience in controlled trials has failed to identify any significant neuroleptic-like activity; however, a syndrome of restlessness, appearing shortly after initiation of treatment, has been reported in some small fraction of buspirone-treated patients. The syndrome may be explained in several ways. For example, buspirone may increase central noradrenergic activity; alternatively, the effect may be attributable to dopaminergic effects (i.e., represent akathisia). See ADVERSE REACTIONS, Postmarketing Experience.

Information for Patients

To assure safe and effective use of buspirone hydrochloride tablets, USP the following information and instructions should be given to patients:

1. Do not take a monoamine oxidase inhibitor (MAOI). Ask your healthcare provider or pharmacist if you are not sure if you take an MAOI, including the antibiotic linezolid.
2. Do not take an MAOI within 2 weeks of stopping buspirone unless directed to do so by your physician.
3. Do not start buspirone if you stopped taking an MAOI in the last 2 weeks unless directed to do so by your physician.
4. Inform your physician about any medications, prescription or non-prescription, alcohol, or drugs that you are now taking or plan to take during your treatment with buspirone hydrochloride tablets, USP.
5. Inform your physician if you are pregnant, or if you are planning to become pregnant, or if you become pregnant while you are taking buspirone hydrochloride tablets, USP.
6. Inform your physician if you are breastfeeding an infant.
7. Until you experience how this medication affects you, do not drive a car or operate potentially dangerous machinery.
8. You should take buspirone hydrochloride tablets, USP consistently, either always with or always without food.
9. During your treatment with buspirone hydrochloride tablets, USP avoid drinking large amounts of grapefruit juice.

Laboratory Tests

There are no specific laboratory tests recommended.

Drug Interactions

Psychotropic Agents

MAO inhibitors: The use of monoamine oxidase inhibitors (MAOIs) intended to treat depression with buspirone or within 14 days of stopping treatment with buspirone is contraindicated because of an increased risk of serotonin syndrome and/or elevated blood pressure. The use of buspirone within 14 days of stopping an MAOI intended to treat depression is also contraindicated.

Starting buspirone in a patient who is being treated with reversible MAOIs such as linezolid or intravenous methylene blue is also contraindicated because of an increased risk of serotonin syndrome. (see WARNINGS, DOSAGE AND ADMINISTRATION AND CONCOMITANT DRUG)

Amitriptyline: After addition of buspirone to the amitriptyline dose regimen, no statistically significant differences in the steady-state pharmacokinetic parameters (Cmax, AUC, and Cmin) of amitriptyline or its metabolite nortriptyline were observed.

Diazepam: After addition of buspirone to the diazepam dose regimen, no statistically significant differences in the steady-state pharmacokinetic parameters (Cmax, AUC, and Cmin) were observed for diazepam, but increases of about 15% were seen for nordiazepam, and minor adverse clinical effects (dizziness, headache, and nausea) were observed.

Haloperidol: In a study in normal volunteers, concomitant administration of buspirone and haloperidol resulted in increased serum haloperidol concentrations. The clinical significance of this finding is not clear.

Nefazodone: (See Inhibitors and Inducers of Cytochrome P450 3A4 [CYP3A4])

Trazodone: There is one report suggesting that the concomitant use of Desyrel® (trazodone hydrochloride) and buspirone may have caused 3- to 6-fold elevations on SGPT (ALT) in a few patients. In a similar study attempting to replicate this finding, no interactive effect on hepatic transaminases was identified.

Triazolam/flurazepam: Coadministration of buspirone with either triazolam or flurazepam did not appear to prolong or intensify the sedative effects of either benzodiazepine.

Other psychotropics: Because the effects of concomitant administration of buspirone with most other psychotropic drugs have not been studied, the concomitant use of buspirone with other CNS-active drugs should be approached with caution.

Inhibitors and Inducers of Cytochrome P450 3A4 (CYP3A4)

Buspirone has been shown in vitroto be metabolized by CYP3A4. This finding is consistent with the in vivointeractions observed between buspirone and the following:

Diltiazem and verapamil:In a study of nine healthy volunteers, coadministration of buspirone (10 mg as a single dose) with verapamil (80 mg t.i.d.) or diltiazem (60 mg t.i.d.) increased plasma buspirone concentrations (verapamil increased AUC and Cmaxof buspirone 3.4-fold while diltiazem increased AUC and Cmax5.5-fold and 4-fold, respectively). Adverse events attributable to buspirone may be more likely during concomitant administration with either diltiazem or verapamil. Subsequent dose adjustment may be necessary and should be based on clinical assessment.

Erythromycin: In a study in healthy volunteers, coadministration of buspirone (10 mg as a single dose) with erythromycin (1.5 g/day for 4 days) increased plasma buspirone concentrations (5-fold increase in Cmaxand 6-fold increase in AUC). These pharmacokinetic interactions were accompanied by an increased incidence of side effects attributable to buspirone. If the two drugs are to be used in combination, a low dose of buspirone (e.g., 2.5 mg b.i.d.) is recommended. Subsequent dose adjustment of either drug should be based on clinical assessment.

Grapefruit juice: In a study in healthy volunteers, coadministration of buspirone (10 mg as a single dose) with grapefruit juice (200 mL double-strength t.i.d. for 2 days) increased plasma buspirone concentrations (4.3-fold increase in Cmax; 9.2-fold increase in AUC). Patients receiving buspirone should be advised to avoid drinking such large amounts of grapefruit juice.

Itraconazole: In a study in healthy volunteers, coadministration of buspirone (10 mg as a single dose) with itraconazole (200 mg/day for 4 days) increased plasma buspirone concentrations (13-fold increase in Cmaxand 19-fold increase in AUC). These pharmacokinetic interactions were accompanied by an increased incidence of side effects attributable to buspirone. If the two drugs are to be used in combination, a low dose of buspirone (e.g., 2.5 mg q.d.) is recommended. Subsequent dose adjustment of either drug should be based on clinical assessment.

Nefazodone: In a study of steady-state pharmacokinetics in healthy volunteers, coadministration of buspirone (2.5 or 5 mg b.i.d.) with nefazodone (250 mg b.i.d.) resulted in marked increases in plasma buspirone concentrations (increases up to 20-fold in Cmaxand up to 50-fold in AUC) and statistically significant decreases (about 50%) in plasma concentrations of the buspirone metabolite 1-PP. With 5 mg b.i.d. doses of buspirone, slight increases in AUC were observed for nefazodone (23%) and its metabolites hydroxynefazodone (HO-NEF) (17%) and meta-chlorophenylpiperazine (9%). Slight increases in Cmaxwere observed for nefazodone (8%) and its metabolite HO-NEF (11%). Subjects receiving buspirone 5 mg b.i.d. and nefazodone 250 mg b.i.d. experienced lightheadedness, asthenia, dizziness, and somnolence, adverse events also observed with either drug alone. If the two drugs are to be used in combination, a low dose of buspirone (e.g., 2.5 mg q.d.) is recommended. Subsequent dose adjustment of either drug should be based on clinical assessment.

Rifampin: In a study in healthy volunteers, coadministration of buspirone (30 mg as a single dose) with rifampin (600 mg/day for 5 days) decreased the plasma concentrations (83.7% decrease in Cmax; 89.6% decrease in AUC) and pharmacodynamic effects of buspirone. If the two drugs are to be used in combination, the dosage of buspirone may need adjusting to maintain anxiolytic effect.

Other inhibitors and inducers of CYP3A4: Substances that inhibit CYP3A4, such as ketoconazole or ritonavir, may inhibit buspirone metabolism and increase plasma concentrations of buspirone while substances that induce CYP3A4, such as dexamethasone or certain anticonvulsants (phenytoin, phenobarbital, carbamazepine), may increase the rate of buspirone metabolism. If a patient has been titrated to a stable dosage on buspirone, a dose adjustment of buspirone may be necessary to avoid adverse events attributable to buspirone or diminished anxiolytic activity. Consequently, when administered with a potent inhibitor of CYP3A4, a low dose of buspirone used cautiously is recommended. When used in combination with a potent inducer of CYP3A4 the dosage of buspirone may need adjusting to maintain anxiolytic effect.

Other Drugs

Cimetidine: Coadministration of buspirone with cimetidine was found to increase Cmax(40%) and Tmax(2-fold), but had minimal effects on the AUC of buspirone.

Protein Binding

In vitro, buspirone does not displace tightly bound drugs like phenytoin, propranolol, and warfarin from serum proteins. However, there has been one report of prolonged prothrombin time when buspirone was added to the regimen of a patient treated with warfarin. The patient was also chronically receiving phenytoin, phenobarbital, digoxin, and Synthroid®. In vitro, buspirone may displace less firmly bound drugs like digoxin. The clinical significance of this property is unknown.

Therapeutic levels of aspirin, desipramine, diazepam, flurazepam, ibuprofen, propranolol, thioridazine, and tolbutamide had only a limited effect on the extent of binding of buspirone to plasma proteins (see CLINICAL PHARMACOLOGY).

Drug/Laboratory Test Interactions

Buspirone hydrochloride may interfere with the urinary metanephrine/ catecholamine assay. It has been mistakenly read as metanephrine during routine assay testing for pheochromocytoma, resulting in a false positive laboratory result. Buspirone hydrochloride should therefore be discontinued for at least 48 hours prior to undergoing a urine collection for catecholamines.

Carcinogenesis, Mutagenesis, Impairment of Fertility

No evidence of carcinogenic potential was observed in rats during a 24-month study at approximately 133 times the maximum recommended human oral dose; or in mice, during an 18 month study at approximately 167 times the maximum recommended human oral dose.

With or without metabolic activation, buspirone did not induce point mutations in five strains of Salmonella typhimurium(Ames Test) or mouse lymphoma L5178YTK+ cell cultures, nor was DNA damage observed with buspirone in Wi-38 human cells. Chromosomal aberrations or abnormalities did not occur in bone marrow cells of mice given one or five daily doses of buspirone.

Pregnancy: Teratogenic Effects

No fertility impairment or fetal damage was observed in reproduction studies performed in rats and rabbits at buspirone doses of approximately 30 times the maximum recommended human dose. In humans, however, adequate and well-controlled studies during pregnancy have notbeen performed. Because animal reproduction studies are not always predictive of human response, this drug should be used during pregnancy only if clearly needed.

Labor and Delivery

The effect of buspirone hydrochloride, USP on labor and delivery in women is unknown. No adverse effects were noted in reproduction studies in rats.

Nursing Mothers

The extent of the excretion in human milk of buspirone or its metabolites is not known. In rats, however, buspirone and its metabolites are excreted in milk. Buspirone hydrochloride tablets, USP administration to nursing women should be avoided if clinically possible.

Pediatric Use

The safety and effectiveness of buspirone were evaluated in two placebo-controlled 6-week trials involving a total of 559 pediatric patients (ranging from 6 to 17 years of age) with GAD. Doses studied were 7.5 mg to 30 mg b.i.d. (15 to 60 mg/day). There were no significant differences between buspirone and placebo with regard to the symptoms of GAD following doses recommended for the treatment of GAD in adults. Pharmacokinetic studies have shown that, for identical doses, plasma exposure to buspirone and its active metabolite, 1-PP, are equal to or higher in pediatric patients than adults. No unexpected safety findings were associated with buspirone in these trials. There are no long-term safety or efficacy data in this population.

Geriatric Use

In one study of 6632 patients who received buspirone for the treatment of anxiety, 605 patients were ≥ 65 years old and 41 were ≥ 75 years old; the safety and efficacy profiles for these 605 elderly patients (mean age = 70.8 years) were similar to those in the younger population (mean age = 43.3 years). Review of spontaneously reported adverse clinical events has not identified differences between elderly and younger patients, but greater sensitivity of some older patients cannot be ruled out.

There were no effects of age on the pharmacokinetics of buspirone (see CLINICAL PHARMACOLOGY: Special Populations).

Use in Patients With Impaired Hepatic or Renal Function

Buspirone is metabolized by the liver and excreted by the kidneys. A pharmacokinetic study in patients with impaired hepatic or renal function demonstrated increased plasma levels and a lengthened half-life of buspirone. Therefore, the administration of buspirone hydrochloride tablets, USP to patients with severe hepatic or renal impairment cannot be recommended (see CLINICAL PHARMACOLOGY).

ADVERSE REACTIONS (See also PRECAUTIONS)

Commonly Observed

The more commonly observed untoward events associated with the use of buspirone hydrochloride tablets, USP not seen at an equivalent incidence among placebo-treated patients include dizziness, nausea, headache, nervousness, lightheadedness, and excitement.

Associated with Discontinuation of Treatment

One guide to the relative clinical importance of adverse events associated with buspirone hydrochloride tablets, USP is provided by the frequency with which they caused drug discontinuation during clinical testing. Approximately 10% of the 2200 anxious patients who participated in the buspirone hydrochloride tablets, USP premarketing clinical efficacy trials in anxiety disorders lasting 3 to 4 weeks discontinued treatment due to an adverse event. The more common events causing discontinuation included: central nervous system disturbances (3.4%), primarily dizziness, insomnia, nervousness, drowsiness, and lightheaded feeling; gastrointestinal disturbances (1.2%), primarily nausea; and miscellaneous disturbances (1.1%), primarily headache and fatigue. In addition, 3.4% of patients had multiple complaints, none of which could be characterized as primary.

Incidence in Controlled Clinical Trials

The tablethat follows enumerates adverse events that occurred at a frequency of 1% or more among buspirone hydrochloride, USP patients who participated in 4-week, controlled trials comparing buspirone hydrochloride tablets, USP with placebo. The frequencies were obtained from pooled data for 17 trials. The prescriber should be aware that these figures cannot be used to predict the incidence of side effects in the course of usual medical practice where patient characteristics and other factors differ from those which prevailed in the clinical trials. Similarly, the cited frequencies cannot be compared with figures obtained from other clinical investigations involving different treatments, uses, and investigators. Comparison of the cited figures, however, does provide the prescribing physician with some basis for estimating the relative contribution of drug and nondrug factors to the side-effect incidence rate in the population studied.

TREATMENT-EMERGENT ADVERSE EXPERIENCE
INCIDENCE IN PLACEBO-CONTROLLED CLINICAL TRIALS*
(Percent of Patients Reporting)
Adverse Experience | Buspirone HCL (n=477) | Placebo (n=464)
Cardiovascular
Tachycardia/Palpitations | 1 | 1
CNS
Dizziness | 12 | 3
Drowsiness | 10 | 9
Nervousness | 5 | 1
Insomnia | 3 | 3
Lightheadedness | 3 | -
Decreased Concentration | 2 | 2
Excitement | 2 | -
Anger/Hostility | 2 | -
Confusion | 2 | -
Depression | 2 | 2
EENT
Blurred Vision | 2 | -
Gastrointestinal
Nausea | 8 | 5
Dry Mouth | 3 | 4
Abdominal/Gastric Distress | 2 | 2
Diarrhea | 2 | -
Constipation | 1 | 2
Vomiting | 1 | 2
Musculoskeletal
Musculoskeletal Aches/Pains | 1 | -
Neurological
Numbness | 2 | -
Paresthesia | 1 | -
Incoordination | 1 | -
Tremor | 1 | -
Skin
Skin Rash | 1 | -
Miscellaneous
Headache | 6 | 3
Fatigue | 4 | 4
Weakness | 2 | -
Sweating/Clamminess | 1 | -
* Events reported by at least 1% of buspirone hydrochloride tablets
patients are included.
– Incidence less than 1%.

Other Events Observed During the Entire Premarketing Evaluation of Buspirone Hydrochloride Tablets, USP

During its premarketing assessment, buspirone hydrochloride tablets, USP were evaluated in over 3500 subjects. This section reports event frequencies for adverse events occurring in approximately 3000 subjects from this group who took multiple doses of buspirone hydrochloride tablets, USP in the dose range for which buspirone hydrochloride tablets, USP is being recommended (ie, the modal daily dose of buspirone hydrochloride tablets, USP fell between 10 mg and 30 mg for 70% of the patients studied) and for whom safety data were systematically collected. The conditions and duration of exposure to buspirone hydrochloride tablets, USP varied greatly, involving well-controlled studies as well as experience in open and uncontrolled clinical settings. As part of the total experience gained in clinical studies, various adverse events were reported. In the absence of appropriate controls in some of the studies, a causal relationship to buspirone hydrochloride, USP treatment cannot be determined. The list includes all undesirable events reasonably associated with the use of the drug.

The following enumeration by organ system describes events in terms of their relative frequency of reporting in this data base. Events of major clinical importance are also described in the PRECAUTIONSsection.

The following definitions of frequency are used: Frequent adverse events are defined as those occurring in at least 1/100 patients. Infrequent adverse events are those occurring in 1/100 to 1/1000 patients, while rare events are those occurring in less than 1/1000 patients.

Cardiovascular

Frequent was nonspecific chest pain; infrequent were syncope, hypotension, and hypertension; rare were cerebrovascular accident, congestive heart failure, myocardial infarction, cardiomyopathy, and bradycardia.

Central Nervous System

Frequent were dream disturbances; infrequent were depersonalization, dysphoria, noise intolerance, euphoria, akathisia, fearfulness, loss of interest, dissociative reaction, hallucinations, involuntary movements, slowed reaction time, suicidal ideation, and seizures; rare were feelings of claustrophobia, cold intolerance, stupor, and slurred speech and psychosis.

EENT

Frequent were tinnitus, sore throat, and nasal congestion; infrequent were redness and itching of the eyes, altered taste, altered smell, and conjunctivitis; rare were inner ear abnormality, eye pain, photophobia, and pressure on eyes.

Endocrine

Rare were galactorrhea and thyroid abnormality.

Gastrointestinal

Infrequent were flatulence, anorexia, increased appetite, salivation, irritable colon, and rectal bleeding; rare was burning of the tongue.

Genitourinary

Infrequent were urinary frequency, urinary hesitancy, menstrual irregularity and spotting, and dysuria; rare were amenorrhea, pelvic inflammatory disease, enuresis, and nocturia.

Musculoskeletal

Infrequent were muscle cramps, muscle spasms, rigid/stiff muscles, and anthralgias; rare was muscle weakness.

Respiratory

Infrequent were hyperventilation, shortness of breath, and chest congestion; rare was epistaxis.

Sexual Function

Infrequent were decreased or increased libido; rare were delayed ejaculation and impotence.

Skin

Infrequent were edema, pruritus, flushing, easy bruising, hair loss, dry skin, facial edema, and blisters; rare were acne and thinning of nails.

Clinical Laboratory

Infrequent were increases in hepatic aminotransferases (SGOT, SGPT); rare were eosinophilia, leukopenia, and thrombocytopenia.

Miscellaneous

Infrequent were weight gain, fever, roaring sensation in the head, weight loss, and malaise; rare were alcohol abuse, bleeding disturbance, loss of voice, and hiccoughs.

Postmarketing Experience

Postmarketing experience has shown an adverse experience profile similar to that given above. Voluntary reports since introduction have included rare occurrences of allergic reactions (including urticaria), angioedema, cogwheel rigidity, dizziness (rarely reported as vertigo), dystonic reactions (including dystonia), ataxias, extrapyramidal symptoms, dyskinesias (acute and tardive), ecchymosis, emotional lability, serotonin syndrome, transient difficulty with recall, urinary retention, visual changes (including tunnel vision), parkinsonism, akathisia, restless leg syndrome, and restlessness. Because of the uncontrolled nature of these spontaneous reports, a causal relationship to buspirone hydrochloride tablets, USP treatment has not been determined.

DRUG ABUSE AND DEPENDENCE

Controlled Substance Class

Buspirone hydrochloride, USP is not a controlled substance.

Physical and Psychological Dependence

In human and animal studies, buspirone has shown no potential for abuse or diversion and there is no evidence that it causes tolerance, or either physical or psychological dependence. Human volunteers with a history of recreational drug or alcohol usage were studied in two double-blind clinical investigations. None of the subjects were able to distinguish between buspirone hydrochloride tablets, USP and placebo. By contrast, subjects showed a statistically significant preference for methaqualone and diazepam. Studies in monkeys, mice, and rats have indicated that buspirone lacks potential for abuse.

Following chronic administration in the rat, abrupt withdrawal of buspirone did not result in the loss of body weight commonly observed with substances that cause physical dependency.

Although there is no direct evidence that buspirone hydrochloride tablets, USP cause physical dependence or drug-seeking behavior, it is difficult to predict from experiments the extent to which a CNS-active drug will be misused, diverted, and/or abused once marketed. Consequently, physicians should carefully evaluate patients for a history of drug abuse and follow such patients closely, observing them for signs of buspirone hydrochloride tablets, USP misuse or abuse (e.g., development of tolerance, incrementation of dose, drug-seeking behavior).

OVERDOSAGE

Signs and Symptoms

In clinical pharmacology trials, doses as high as 375 mg/day were administered to healthy male volunteers. As this dose was approached, the following symptoms were observed: nausea, vomiting, dizziness, drowsiness, miosis, and gastric distress. A few cases of overdosage have been reported, with complete recovery as the usual outcome. No deaths have been reported following overdosage with buspirone hydrochloride tablets, USP alone. Rare cases of intentional overdosage with a fatal outcome were invariably associated with ingestion of multiple drugs and/or alcohol, and a causal relationship to buspirone could not be determined. Toxicology studies of buspirone yielded the following LD50values: mice, 655 mg/kg; rats, 196 mg/kg; dogs, 586 mg/kg; and monkeys, 356 mg/kg. These dosages are 160 to 550 times the recommended human daily dose.

Recommended Overdose Treatment

General symptomatic and supportive measures should be used along with immediate gastric lavage. Respiration, pulse, and blood pressure should be monitored as in all cases of drug overdosage. No specific antidote is known to buspirone, and dialyzability of buspirone has not been determined.

DOSAGE AND ADMINISTRATION

The recommended initial dose is 15 mg daily (7.5 mg b.i.d.). To achieve an optimal therapeutic response, at intervals of 2 to 3 days the dosage may be increased 5 mg per day, as needed. The maximum daily dosage should not exceed 60 mg per day. In clinical trials allowing dose titration, divided doses of 20 mg to 30 mg per day were commonly employed.

The bioavailability of buspirone is increased when given with food as compared to the fasted state (see CLINICAL PHARMACOLOGY). Consequently, patients should take buspirone in a consistent manner with regard to the timing of dosing; either always with or always without food.

When buspirone is to be given with a potent inhibitor of CYP3A4, the dosage recommendations described in the PRECAUTIONS: Drug Interactions section should be followed.

Switching a Patient To or From a Monoamine Oxidase Inhibitor (MAOI) Antidepressant

At least 14 days should elapse between discontinuation of an MAOI intended to treat depression and initiation of therapy with buspirone hydrochloride tablets, USP. Conversely, at least 14 days should be allowed after stopping buspirone hydrochloride tablets, USP before starting an MAOI antidepressant (see CONTRAINDICATIONSand DRUG INTERACTIONS).

Use of buspirone hydrochloride tablets, USP with (Reversible) MAOIs, Such as Linezolid or Methylene Blue

Do not start buspirone hydrochloride tablets, USP in a patient who is being treated with a reversible MAOI such as linezolid or intravenous methylene blue because there is an increased risk of serotonin syndrome. In a patient who requires more urgent treatment of a psychiatric condition, non-pharmacological interventions, including hospitalization, should be considered (see CONTRAINDICATIONSand DRUG INTERACTIONS).

In some cases, a patient already receiving therapy with buspirone hydrochloride tablets, USP may require urgent treatment with linezolid or intravenous methylene blue. If acceptable alternatives to linezolid or intravenous methylene blue treatment are not available and the potential benefits of linezolid or intravenous methylene blue treatment are judged to outweigh the risks of serotonin syndrome in a particular patient, buspirone hydrochloride tablets, USP should be stopped promptly, and linezolid or intravenous methylene blue can be administered. The patient should be monitored for symptoms of serotonin syndrome for 2 weeks or until 24 hours after the last dose of linezolid or intravenous methylene blue, whichever comes first. Therapy with buspirone hydrochloride tablets, USP may be resumed 24 hours after the last dose of linezolid or intravenous methylene blue (see WARNINGS).

The risk of administering methylene blue by non-intravenous routes (such as oral tablets or by local injection) or in intravenous doses much lower than 1 mg per kg with buspirone hydrochloride tablets, USP is unclear. The clinician should, nevertheless, be aware of the possibility of emergent symptoms of serotonin syndrome with such use (see CONTRAINDICATIONS, WARNINGSand DRUG INTERACTIONS).

HOW SUPPLIED:

Buspirone Hydrochloride Tablets, USP 5 mgare white to off-white, round, flat-faced, beveled edge bisected tablets debossed “091” above the bisect on one side and "O" logo on the other side.

Supplied in bottles of 60's (NDC 72789-139-60), 100’s (NDC 72789-139-01) .

Buspirone Hydrochloride Tablets, USP 10 mgare white to off-white, round, flat-faced, beveled edge bisected tablets debossed “092” above the bisect on one side and "O" logo on the other side.

Supplied in bottles of 100’s (NDC 72789-140-01).

Buspirone Hydrochloride Tablets, USP 15 mgare white rectangle, flat faced, beveled edge tablets double-scored and debossed with "0|9|3" on one side and double-scored and debossed "|O|" logo on the other side.

Supplied in bottles of 100’s (NDC 72789-141-01) .

Buspirone Hydrochloride Tablets, USP 30 mgare white to off-white, capsule shape, flat face, beveled edge tablets, scored and debossed “094 O” on one side and double-scored and debossed “10 10 10” on the other side.

Supplied in bottles of 60’s (NDC 72789-142-60), 100’s (NDC 72789-142-01).

Dispense 15 mg and 30 mg with Patient Information Sheet available at: https://www.oxford-rx.com/med-guides

Store at 25°C (77°F); excursions permitted between 15°C to 30°C (59°F to 86°F) [see USP controlled room temperature].

Dispense in a tight, light-resistant container (USP).

REFERENCE

1. American Psychiatric Association, Ed.: Diagnostic and Statistical Manual of Mental Disorders—III, American Psychiatric Association, May 1980.

Synthroid® is the registered trademark of Abbott Laboratories.

Manufactured by:
Oxford Pharmaceuticals LLC
301 Leaf Lake Parkway
Birmingham, AL 35211 USA

8200017
06/2025
R04

Patient Information Sheet
BUSPIRONE HYDROCHLORIDE, USP
Rx Only
Dispense with Patient Information Sheet available at:
https://www.oxford-rx.com/med-guides
HOW TO USE:
Buspirone Hydrochloride Tablets, USP
15 mg and 30 mg Tablets
in convenient adjustable dosage tablet form

Response to buspirone varies among individuals. Your physician may find it necessary to adjust your dosage to obtain the proper response.

This adjustable dosage tablet design makes dosage adjustments easy. Each tablet is scored and can be broken accurately to provide any of the following dosages.

If your doctor prescribed
the 30-mg tablet:

If your doctor prescribed
the 15-mg tablet:

30 mg
(the entire tablet)

15 mg
(the entire tablet)

20 mg
(two thirds of a tablet)

10 mg
(two thirds of a tablet)

10 mg
(one third of a tablet)

5 mg
(one third of a tablet)

15 mg
(one half of a tablet)

7.5 mg
(one half of a tablet)

To break a adjustable dosage tablet accurately and easily, hold the tablet between your thumbs and index fingers close to the appropriate tablet score (groove) as shown in the photo. Then, with the tablet score facing you, apply pressure and snap the tablet segments apart (segments breaking incorrectly should not be used).

PATIENT INFORMATION

Manufactured by: Oxford Pharmaceuticals LLC
301 Leaf Lake Parkway, Birmingham, AL 35211 USA
8200016
02/22
R02

Principal Display Panel

BusPIRone
Hydrochloride
Tablets, USP
5 mg
Rx only

BusPIRone
Hydrochloride
Tablets, USP
10 mg
Rx only

BusPIRone
Hydrochloride
Tablets, USP
15 mg
PHARMACIST: DISPENSE WITH PATIENT
INFORMATION SHEET
Rx only

BusPIRone
Hydrochloride
Tablets, USP
30 mg
PHARMACIST: DISPENSE WITH PATIENT
INFORMATION SHEET
Rx only